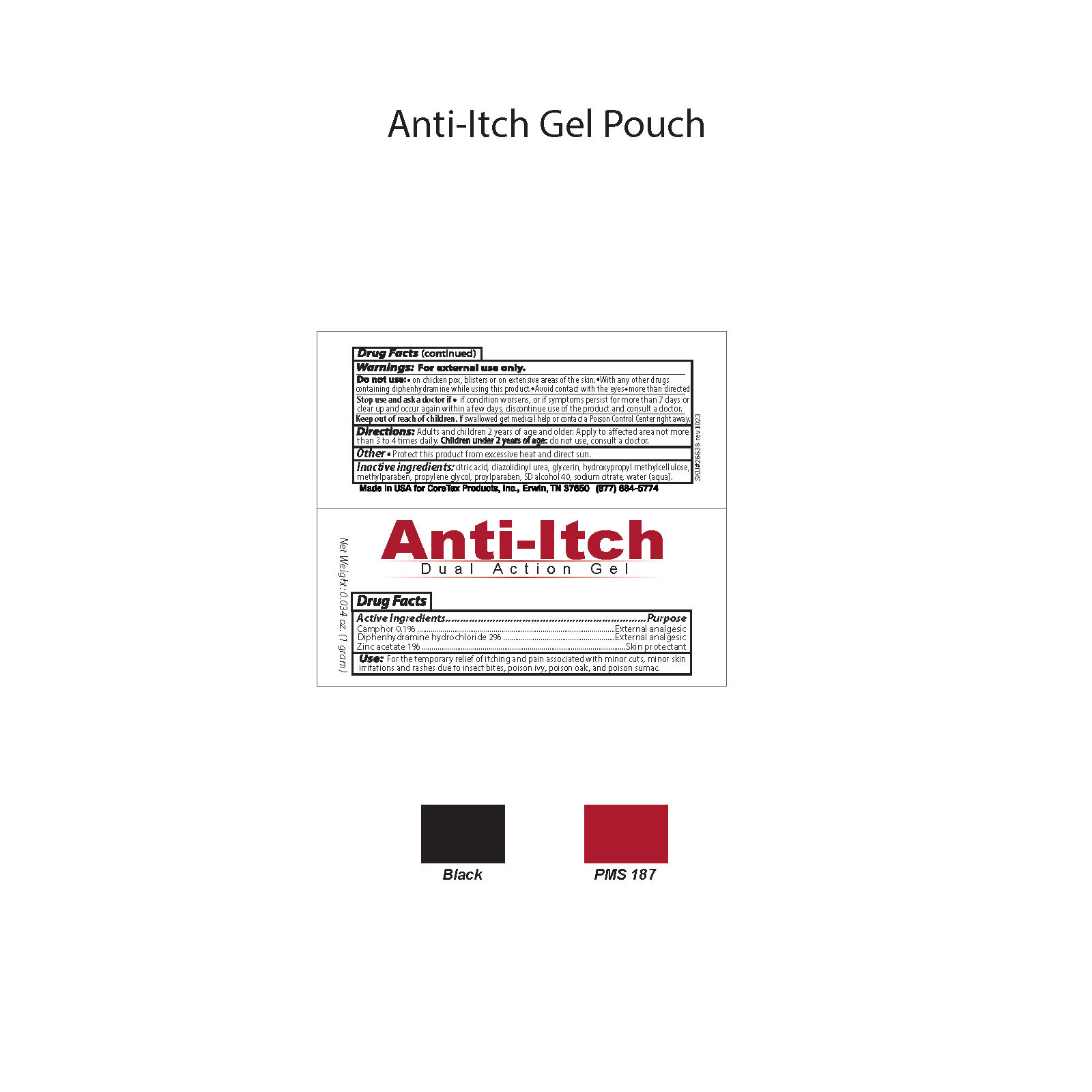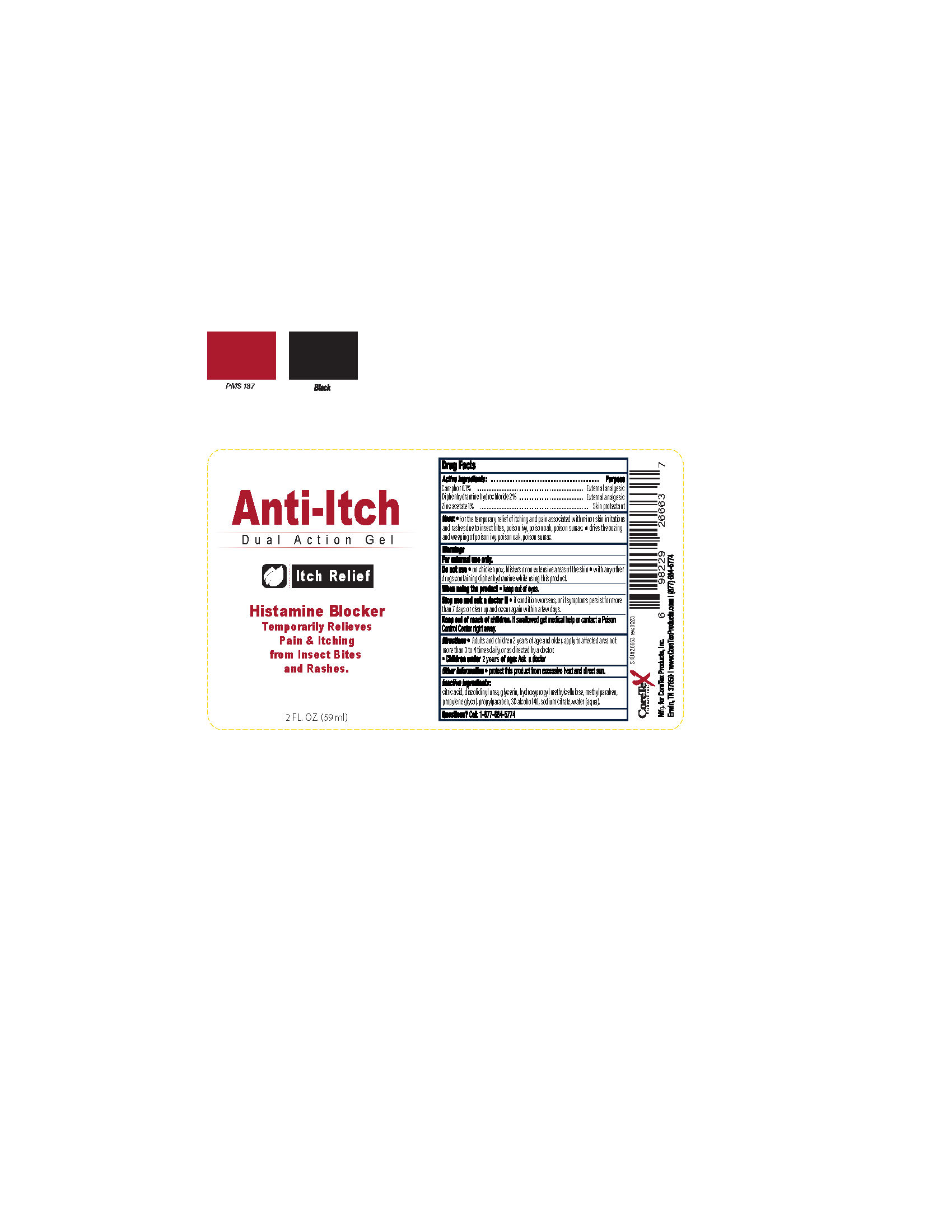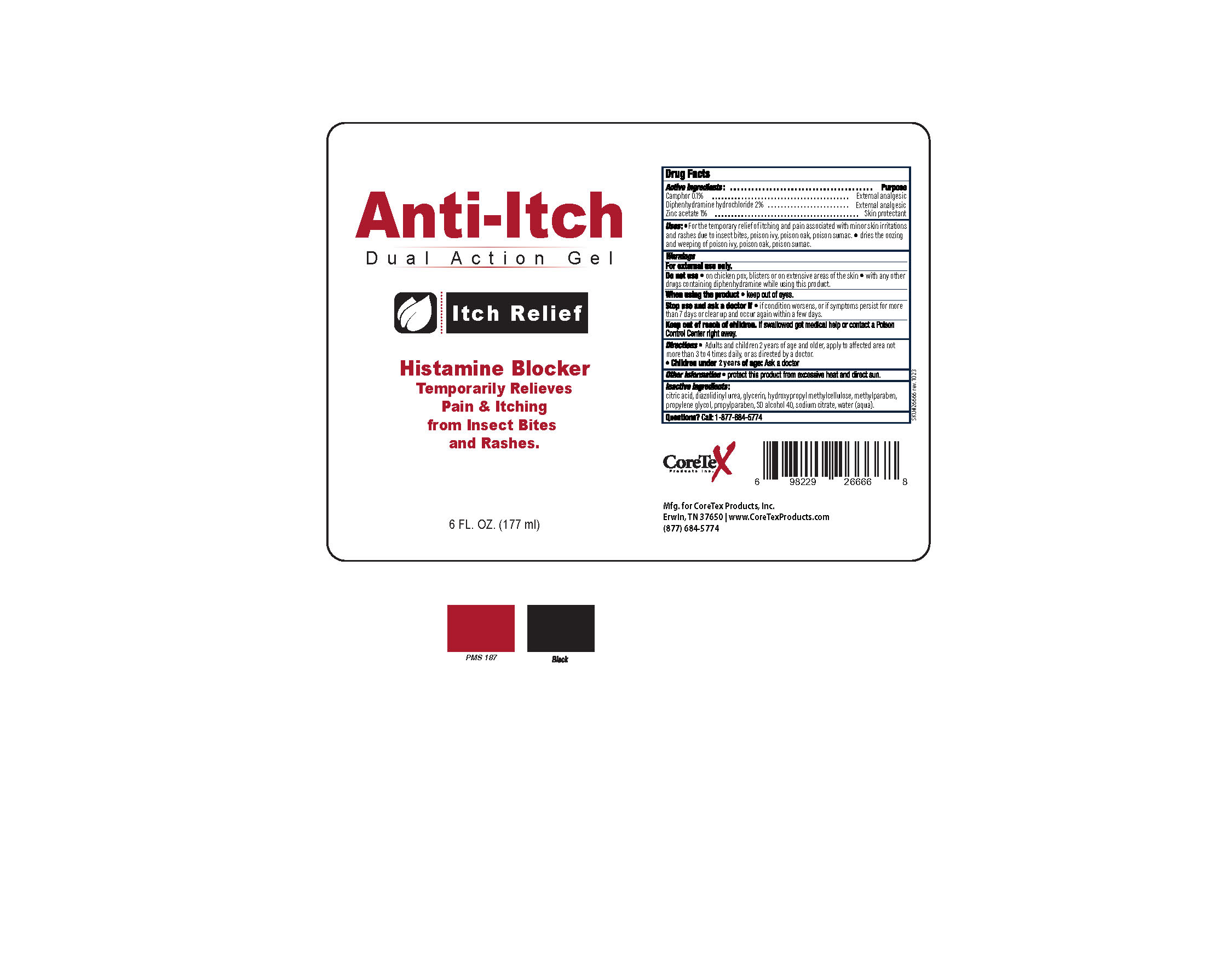 DRUG LABEL: CoreTex Anti-Itch Gel
NDC: 65753-400 | Form: GEL
Manufacturer: CoreTex Products Inc
Category: otc | Type: HUMAN OTC DRUG LABEL
Date: 20241006

ACTIVE INGREDIENTS: DIPHENHYDRAMINE HYDROCHLORIDE 2 g/100 mL; ZINC ACETATE 1 g/100 mL; CAMPHOR (SYNTHETIC) 0.1 g/100 mL
INACTIVE INGREDIENTS: METHYLCELLULOSE (1500 CPS); PROPYLPARABEN; GLYCERIN; PROPYLENE GLYCOL 1-ALLYL ETHER; SODIUM CITRATE; DIAZOLIDINYL UREA; METHYLPARABEN; ALCOHOL; WATER; ANHYDROUS CITRIC ACID

Cortex Anti-Itch Gel
65753-400

Active Ingredients

Camphor 0.1%

Diphenhydramine hydrochloride 2%

Zinc acetate 1%

Purpose

Extrenal analgesic

External analgesic

Skin protectant

Uses

- For the temporary relief of itching and pain associated with minor cuts, minor skin irritations and rashes due to insect bites, poison ivy, poison oak, and poison sumac.

Warnings

For external use only.

Do Not Use

- on chicken pox, blisters or on extensive areas of the skin
- with any drugs containing diphenhydramine while using this product.
- Avoid contact with the eyes
- more than directed

When using the product:

- Keep out of eyes.

Stop use and ask a doctor if

- conditions worsen or if symptoms persist for more than 7 days or clear up and occur again within a few days.

Keep out of reach of children.

If swallowed get medical help or contact Poison Control center right away.

Directions

Adults and children 2 years of age and older: apply to affected area not more than 3 to 4 times daily. Children under 2 years of age:do not use, consult a doctor.

Other Information

- protect this product from excessive heat and direct sun.

Inactive Ingredients

citric acid, diazolidinyl urea, glycerin, hydroxypropyl methylcellulose, methylparaben, propylene glycol, propylparaben, SD alcohol 40, sodium citrate, water (aqua).

Questions?

Call: (877) 684-5774

Made in USA for CoreTex Products, Inc. Erwin, TN 37650 (877) 684-5774